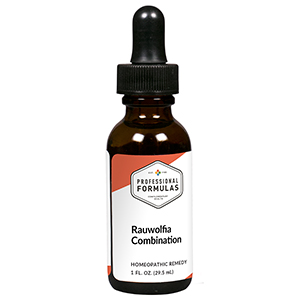 DRUG LABEL: Rauwolfia Combination
NDC: 63083-9258 | Form: LIQUID
Manufacturer: Professional Complementary Health Formulas
Category: homeopathic | Type: HUMAN OTC DRUG LABEL
Date: 20190815

ACTIVE INGREDIENTS: HAWTHORN LEAF WITH FLOWER 2 [hp_X]/29.5 mL; CONIUM MACULATUM FLOWERING TOP 3 [hp_X]/29.5 mL; AVISCUMINE 3 [hp_X]/29.5 mL; ARNICA MONTANA WHOLE 4 [hp_X]/29.5 mL; KALMIA LATIFOLIA LEAF 4 [hp_X]/29.5 mL; AMARYLLIS BELLADONNA WHOLE 6 [hp_X]/29.5 mL; LYCOPODIUM CLAVATUM SPORE 6 [hp_X]/29.5 mL; RAUWOLFIA SERPENTINA 6 [hp_X]/29.5 mL; ARTICHOKE 8 [hp_X]/29.5 mL; MELILOTUS OFFICINALIS TOP 8 [hp_X]/29.5 mL; GOLD MONOIODIDE 10 [hp_X]/29.5 mL; SULFUR 10 [hp_X]/29.5 mL
INACTIVE INGREDIENTS: ALCOHOL; WATER

R258

ACTIVE INGREDIENTS

Crataegus oxyacantha 2X
Conium maculatum 3X
Viscum album 3X
Arnica montana 4X
Kalmia latifolia 4X
Belladonna 6X
Lycopodium clavatum 6X
Rauwolfia serpentina 6X
Cynara scolymus 8X
Melilotus officinalis 8X
Aurum iodatum 10X
Sulphur 10X

QUESTIONS

Professional Formulas

PO Box 2034 Lake Oswego, OR 97035

INDICATIONS

For the temporary relief of headache, dizziness, or vertigo particularly with smoking, excessive drinking of alcohol, obesity, or a poor diet.*

PURPOSE

*Claims based on traditional homeopathic practice, not accepted medical evidence. Not FDA evaluated.

WARNINGS

In case of overdose, get medical help or contact a poison control center right away.

Keep out of the reach of children.

PREGNANCY OR BREAST FEEDING

If pregnant or breastfeeding, ask a healthcare professional before use.

DIRECTIONS

Place drops under tongue 30 minutes before/after meals. Adults and children 12 years and over: Take 10 drops up to 3 times per day. Consult a physician for use in children under 12 years of age.

OTHER INFORMATION

Tamper resistant. If seal is broken, do not use. After opening, close container tightly and store at room temperature away from heat.

INACTIVE INGREDIENTS

40% ethanol, purified water.

LABEL

Est 1985

Professional Formulas

Complementary Health

Rauwolfia Combination

Homeopathic Remedy

1 FL. OZ. (29.5 mL)